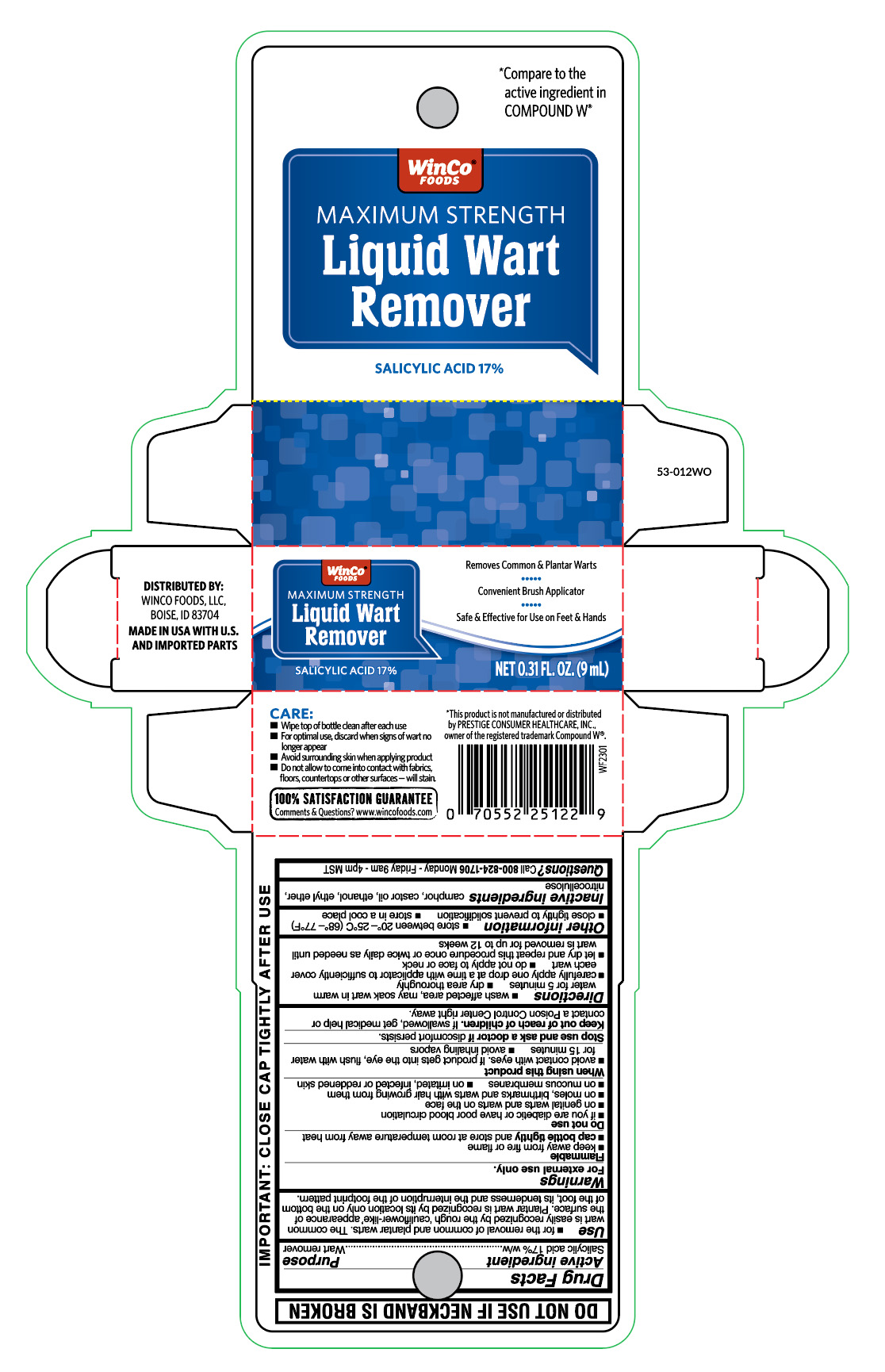 DRUG LABEL: Liquid Wart Remover
NDC: 67091-752 | Form: LIQUID
Manufacturer: WinCo Foods LLC
Category: otc | Type: HUMAN OTC DRUG LABEL
Date: 20251007

ACTIVE INGREDIENTS: SALICYLIC ACID 170 mg/1 mL
INACTIVE INGREDIENTS: PYROXYLIN; CAMPHOR (SYNTHETIC); CASTOR OIL; ETHER; ALCOHOL

WinCo Liquid Wart Remover

Active ingredient

Salicylic acid 17% w/w

Purpose

Wart remover

Uses

- for the removal of common and plantar warts. The common wart is easily recognized by the rough 'cauliflower-like' appearance of the surface. Plantar wart is recognized by its location only on the bottom of the foot, its tenderness and the interruption of the footprint pattern.

Warnings

For external use only.

Flammable

- keep away from fire or flame
- cap bottle tightly and store at room temerature away from heat

Do not use

- if you are diabetic or have poor blood circulation
- on genital warts and warts on the face
- on moles, birthmarks and warts with hair growing from them
- on mucous membranes
- on irritated, infected or reddened skin

When using this product

- avoid contact with eyes. If product gets into the eye, flush with water for 15 minutes
- avoid inhaling vapors

Stop use and ask doctor if

discomfort persists.

Keep out of reach of children.

If swallowed, get medical help or contact a Poison Control Center right away.

Directions

- wash affected area, may soak wart in warm water for 5 minutes
- dry area thoroughly
- carefully apply one drop at a time with applicator to sufficiently cover each wart
- do not apply to face or neck
- let dry and repeat this procedure once or twice daily as needed until wart is removed for up to 12 weeks

Other information

store between 20° to 25°C (68° - 77°F)

- close tightly to prevent solidification
- store in a cool place

Inactive ingredients

camphor, castor oil, ethanol, ethyl ether, nitrocellulose

Questions?

Call 800-824-1706 Monday-Friday 9am-4pm MST

Principal Display Panel

WinCO

Foods

MAXIMUM STRENGTH

Liquid Wart

Remover

Salicylic Acid 17%

Removed Common & Plantar Warts

Convenient Brush Applicator

Safe & Effective for Use on Feet & Hands

NET 0.31 FL. OZ. (9mL)